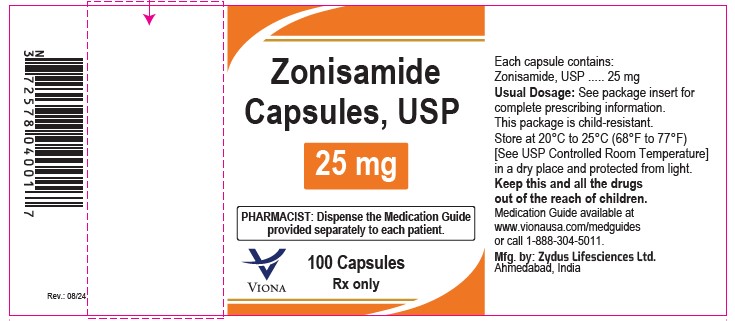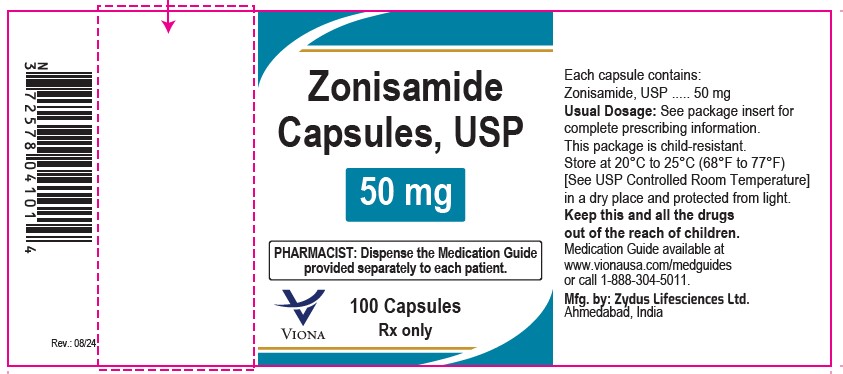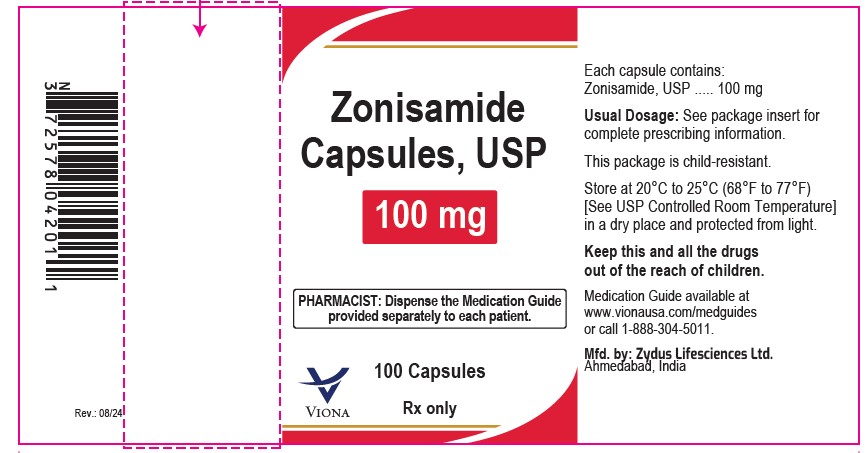 DRUG LABEL: Zonisamide
NDC: 70771-1142 | Form: CAPSULE
Manufacturer: Zydus Lifesciences Limited
Category: prescription | Type: HUMAN PRESCRIPTION DRUG LABEL
Date: 20240816

ACTIVE INGREDIENTS: ZONISAMIDE 25 mg/1 1
INACTIVE INGREDIENTS: FD&C BLUE NO. 1; FD&C RED NO. 4; GELATIN; HYDROGENATED COTTONSEED OIL; CELLULOSE, MICROCRYSTALLINE; SODIUM LAURYL SULFATE; TITANIUM DIOXIDE

Zonisamide Capsules

MEDICATION GUIDE

Manufactured by:

Cadila Healthcare Ltd.

India

PACKAGE LABEL.PRINCIPAL DISPLAY PANEL

NDC 70771-1142-1 in bottle of 100 Capsules

Zonisamide Capsules, 25 mg

Rx only

100 Capsules

NDC 70771-1143-1 in bottle of 100 Capsules

Zonisamide Capsules, 50 mg

Rx only

100 Capsules

NDC 70771-1144-1 in bottle of 100 Capsules

Zonisamide Capsules, 100 mg

Rx only

100 Capsules